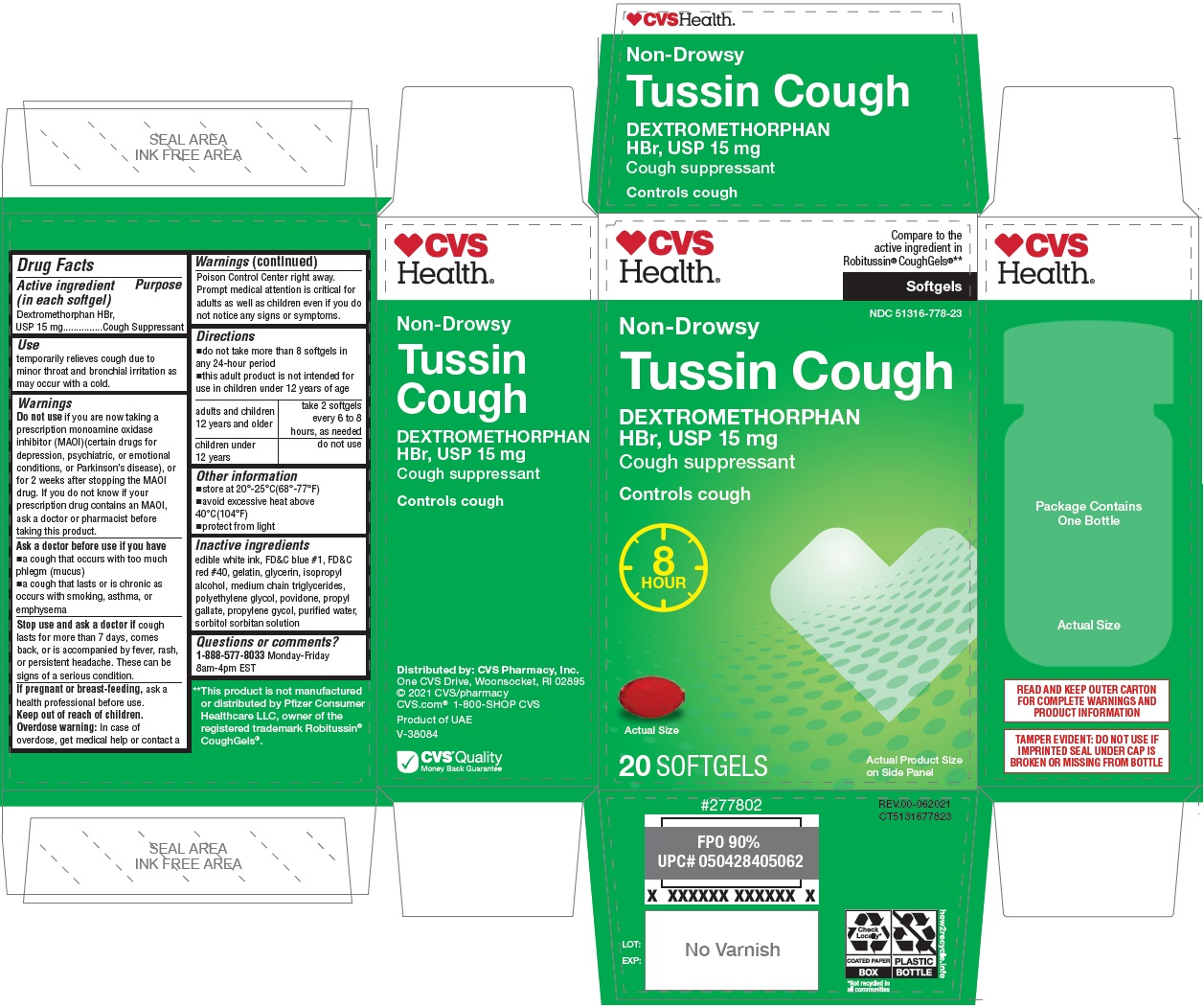 DRUG LABEL: Long Acting Cough Softgels
NDC: 51316-778 | Form: CAPSULE, LIQUID FILLED
Manufacturer: CVS PHARMACY, INC
Category: otc | Type: HUMAN OTC DRUG LABEL
Date: 20250101

ACTIVE INGREDIENTS: DEXTROMETHORPHAN HYDROBROMIDE 15 mg/1 1
INACTIVE INGREDIENTS: FD&C BLUE NO. 1; FD&C RED NO. 40; GELATIN, UNSPECIFIED; GLYCERIN; ISOPROPYL ALCOHOL; MEDIUM-CHAIN TRIGLYCERIDES; POLYETHYLENE GLYCOL, UNSPECIFIED; POVIDONE, UNSPECIFIED; PROPYL GALLATE; PROPYLENE GLYCOL; WATER; SORBITOL; SORBITAN

Long Acting Cough Softgels

Active ingredient (in each softgel)

Dextromethorphan HBr, USP 15mg

Purpose

Cough Suppressant

Use

temporarily relieves cough due to minor throat and bronchial irritation as may occur with a cold.

Warnings

Do not use if you are now taking a prescription monoamine oxidase inhibitor (MAOI) (certain drugs for depression, psychiatric, or emotional conditions, or Parkinson’s disease), or for 2 weeks after stopping the MAOI drug. If you do not know if your prescription drug contains an MAOI, ask a doctor or pharmacist before taking this product.

Ask a doctor before use if you have

- a cough that occurs with too much phlegm (mucus)
- a cough that lasts or is chronic as occurs with smoking, asthma, or emphysema

Stop use and ask a doctor if cough lasts for more than 7 days, comes back, or is accompanied by fever, rash, or persistent headache. These can be signs of a serious condition

If pregnant or breast-feeding, ask a health professional before use.

Keep out of reach of children.
Overdose warning: In case of overdose, get medical help or contact a Poison Control Center right away. Prompt medical attention is critical for adults as well as children even if you do not notice any signs or symptoms.

Directions

- do not take more than 8 softgels in any 24-hour period
- this adult product is not intended for use in children under 12 years of age

adults and children 12 years and older | take 2 softgels every 6 to 8 hours, as needed
children under 12 years | do not use

Other information

- store at 20°-25°C (68°-77°F)
- avoid excessive heat above 40°C (104°F)
- protect from light

Inactive ingredients

edible white ink, FD&C blue #1, FD&C red #40, gelatin, glycerin, isopropyl alcohol, medium chain triglycerides, polyethylene glycol, povidone, propyl gallate, propylene glycol, purified water, sorbitol sorbitan solution

Questions or comments?

1-888-577-8033 Monday-Friday

8am-4pm EST

CVS Health®

Compare to the active ingredient in Robitussin® CoughGels®**

Non-Drowsy

Controls cough

8 HOUR

READ AND KEEP OUTER CARTON FOR COMPLETE WARNINGS AND PRODUCT INFORMATION

TAMPER EVIDENT: DO NOT USE IF IMPRINTED SEAL UNDER CAP IS BROKEN OR MISSING FROM BOTTLE

**This product is not manufactured or distributed by Pfizer Consumer Healthcare LLC, owner of the registered trademark Robitussin® CoughGels®.

Distributed by: CVS Pharmacy, Inc.
One CVS Drive, Woonsocket, RI 02895
© 2021 CVS/pharmacy
CVS.com® 1-800-SHOP CVS
Product of UAE
V-38084

CVS® Quality
Money Back Guarantee